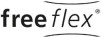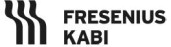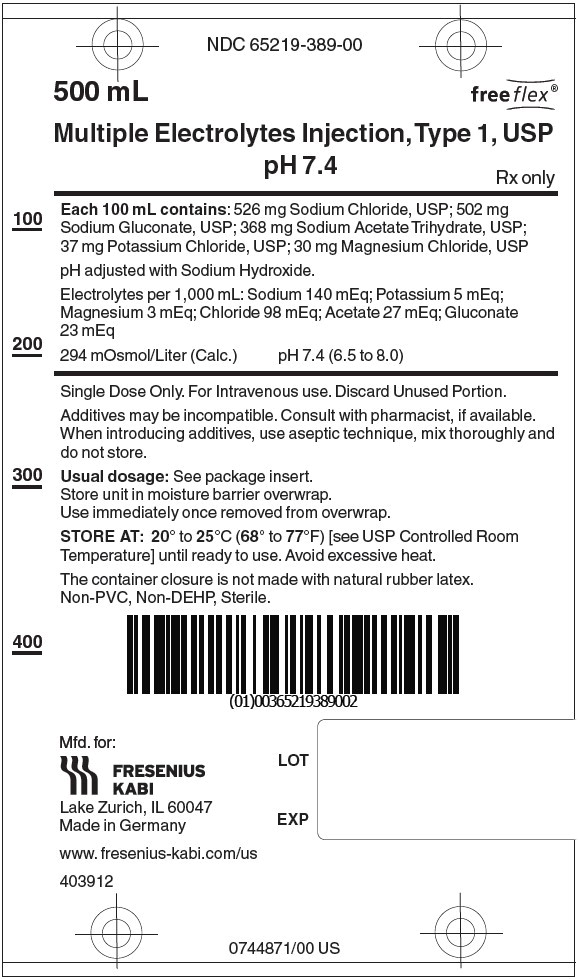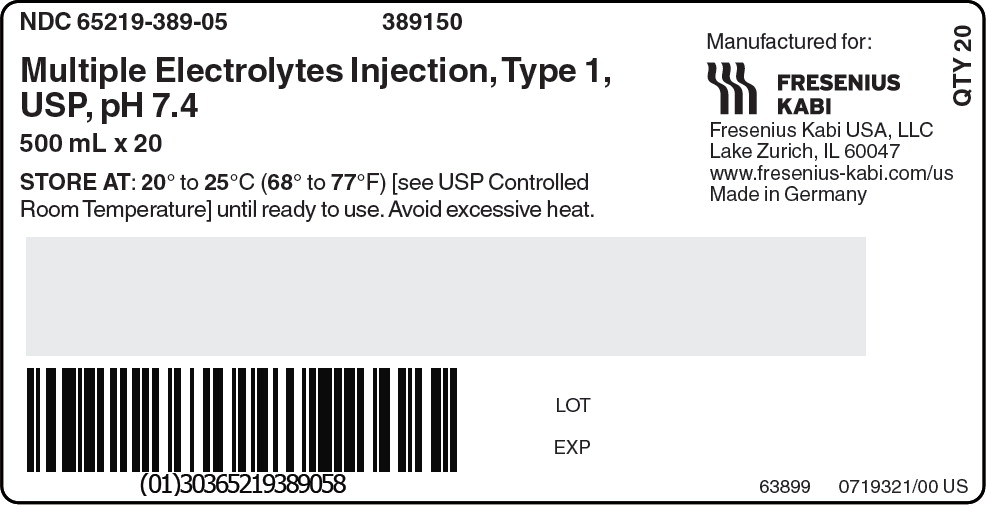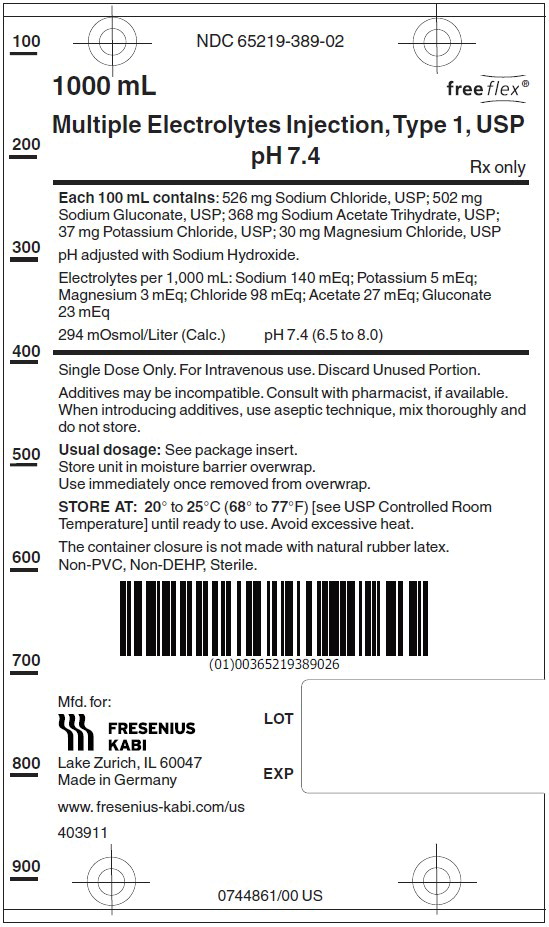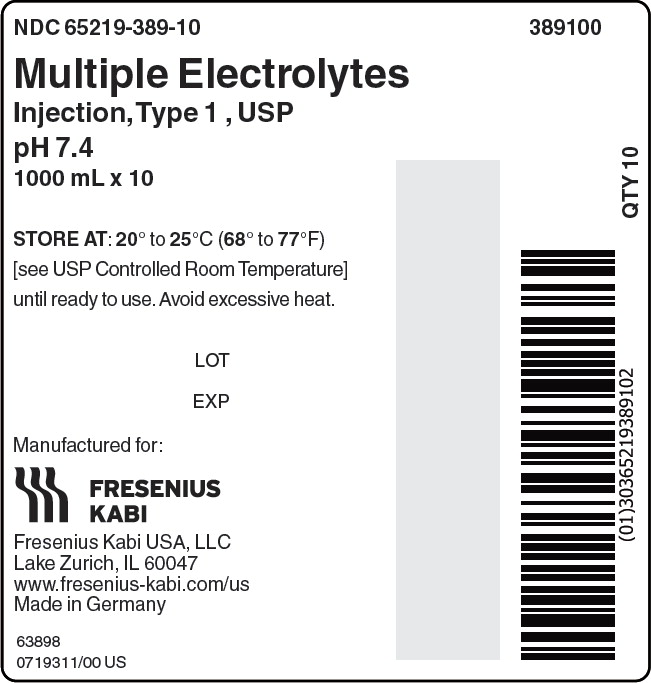 DRUG LABEL: Multiple Electrolytes pH 7.4
NDC: 65219-389 | Form: INJECTION, SOLUTION
Manufacturer: Fresenius Kabi USA, LLC
Category: prescription | Type: HUMAN PRESCRIPTION DRUG LABEL
Date: 20221110

ACTIVE INGREDIENTS: SODIUM CHLORIDE 526 mg/100 mL; SODIUM GLUCONATE 502 mg/100 mL; SODIUM ACETATE 368 mg/100 mL; POTASSIUM CHLORIDE 37 mg/100 mL; MAGNESIUM CHLORIDE 30 mg/100 mL
INACTIVE INGREDIENTS: SODIUM HYDROXIDE

Multiple Electrolytes Injection, Type 1, USP, pH 7.4
in FREEFLEX Plastic Container

DESCRIPTION

Multiple Electrolytes Injection, Type 1, USP, pH 7.4 is a sterile, nonpyrogenic isotonic solution in a single dose container for intravenous administration. Each 100 mL contains 526 mg of Sodium Chloride, USP (NaCl); 502 mg of Sodium Gluconate (C6H11NaO7); 368 mg of Sodium Acetate Trihydrate, USP (C2H3NaO2•3H2O); 37 mg of Potassium Chloride, USP (KCl); and 30 mg of Magnesium Chloride, USP (MgCl2•6H2O). It contains no antimicrobial agents. The pH is adjusted with sodium hydroxide. The pH is 7.4 (6.5 to 8.0).

Multiple Electrolytes Injection, Type 1, USP, pH 7.4 administered intravenously has value as a source of water, electrolytes, and calories. One liter has an ionic concentration of 140 mEq sodium, 5 mEq potassium, 3 mEq magnesium, 98 mEq chloride, 27 mEq acetate, and 23 mEq gluconate. The osmolarity is 294 mOsmol/L (calc). Normal physiologic osmolarity range is 280 to 310 mOsmol/L. The caloric content is 21 kcal/L.

The flexible plastic container is fabricated from a specially formulated non-plasticized, film containing polypropylene and thermoplastic elastomers (freeflex® bag). The amount of water that can permeate from inside the container into the overwrap is insufficient to affect the solution significantly. Solutions in contact with the plastic container can leach out certain of its chemical components in very small amounts within the expiration period. However, the safety of the plastic has been confirmed in tests in animals according to USP biological tests for plastic containers as well as by tissue culture toxicity studies.

CLINICAL PHARMACOLOGY

Multiple Electrolytes Injection, Type 1, USP, pH 7.4 has value as a source of water and electrolytes. It is capable of inducing diuresis depending on the clinical condition of the patient.

Multiple Electrolytes Injection, Type 1, USP, pH 7.4 produces a metabolic alkalinizing effect. Acetate and gluconate ions are metabolized ultimately to carbon dioxide and water, which requires the consumption of hydrogen cations.

INDICATIONS AND USAGE

Multiple Electrolytes Injection, Type 1, USP, pH 7.4 is indicated as a source of water and electrolytes or as an alkalinizing agent.

CONTRAINDICATIONS

Multiple Electrolytes Injection, Type 1, USP, pH 7.4 is contraindicated in patients with a known hypersensitivity to the product. See WARNINGS.

WARNINGS

Hypersensitivity Reactions

Hypersensitivity and infusion reactions have been reported with Multiple Electrolytes Injection, Type 1, USP. See ADVERSE REACTIONS.

Stop the infusion immediately if signs or symptoms of a hypersensitivity reaction develop, such as tachycardia, chest pain, dyspnea and flushing. Appropriate therapeutic countermeasures must be instituted as clinically indicated.

Electrolyte Imbalances

Fluid Overload

Depending on the volume and rate of infusion, the intravenous administration of Multiple Electrolytes Injection, Type 1, USP can cause electrolyte disturbances such as overhydration, and congested states, including pulmonary congestion and edema.

Avoid Multiple Electrolytes Injection, Type 1, USP in patients with or at risk for fluid and/or solute overloading. If use cannot be avoided, monitor fluid balance, electrolyte concentrations, and acid base balance, as needed and especially during prolonged use.

Hyponatremia

Multiple Electrolytes Injection, Type 1, USP may cause hyponatremia. Hyponatremia can lead to acute hyponatremic encephalopathy characterized by headache, nausea, seizures, lethargy, and vomiting. Patients with brain edema are at particular risk of severe, irreversible and life-threatening brain injury.

The risk of hospital-acquired hyponatremia is increased in patients with cardiac or pulmonary failure, and in patients with non-osmotic vasopressin release (including SIADH) treated with high volume of hypotonic Multiple Electrolytes Injection, Type 1, USP.

Avoid Multiple Electrolytes Injection, Type 1, USP in hypervolemic or overhydrated patients. If use cannot be avoided, monitor serum sodium concentrations.

Hypernatremia

Hypernatremia may occur with Multiple Electrolytes Injection, Type 1, USP. Conditions that may increase the risk of hypernatremia, fluid overload and edema (central and peripheral), include patients with: primary hyperaldosteronism; secondary hyperaldosteronism associated with, for example, hypertension, congestive heart failure, liver disease (including cirrhosis), renal disease (including renal artery stenosis, nephrosclerosis); and pre-eclampsia.

Certain medications, such as corticosteroids or corticotropin, may also increase risk of sodium and fluid retention, see PRECAUTIONS.

Avoid Multiple Electrolytes Injection, Type 1, USP in patients with, or at risk for, hypernatremia. If use cannot be avoided, monitor serum sodium concentrations.

Hypermagnesemia

Avoid solutions containing magnesium including Multiple Electrolytes Injection, Type 1, USP in patients with or predisposed to hypermagnesemia, including patients with severe renal impairment and those patients receiving magnesium therapy (e.g., treatment of eclampsia and myasthenia gravis).

Multiple Electrolytes Injection, Type 1, USP is not indicated for the treatment of hypomagnesemia.

Acidosis

Multiple Electrolytes Injection, Type 1, USP is not for use for the treatment of lactic acidosis or severe metabolic acidosis in patients with severe liver and/or renal impairment.

Alkalosis

Excess administration of Multiple Electrolytes Injection, Type 1, USP can result in metabolic alkalosis. Avoid Multiple Electrolytes Injection, Type 1, USP in patients with alkalosis or at risk for alkalosis.

Multiple Electrolytes Injection, Type 1, USP is not indicated for the treatment of hypochloremic hypokalemic alkalosis. Avoid use in patients with hypochloremic hypokalemic alkalosis.

Hypocalcemia

Multiple Electrolytes Injection, Type 1, USP contains no calcium, and an increase in plasma pH due to its alkalinizing effect may lower the concentration of ionized (not protein-bound) calcium. Avoid Multiple Electrolytes Injection, Type 1, USP in patients with hypocalcemia.

Hyperkalemia

Potassium-containing solutions, including Multiple Electrolytes Injection, Type 1, USP may increase the risk of hyperkalemia.

Patient's at increased risk of developing hyperkalemia include those:

- With conditions predisposing to hyperkalemia and/or associated with increased sensitivity to potassium, such as patients with severe renal impairment, acute dehydration, extensive tissue injury or burns, certain cardiac disorders such as congestive heart failure.
- Treated concurrently or recently with agents or products that cause or increase the risk of hyperkalemia (see PRECAUTIONS).

Avoid Multiple Electrolytes Injection, Type 1, USP in patients with, or at risk for hyperkalemia. If use cannot be avoided, monitor serum potassium concentrations.

Although Multiple Electrolytes Injection, Type 1, USP has a potassium concentration in plasma, it is insufficient to produce a useful effect in case of severe potassium deficiency; therefore, it is not indicated for correction of severe potassium deficiency.

PRECAUTIONS

Patients with Renal Impairment

In patients with renal impairment, administration of Multiple Electrolytes Injection, Type 1, USP may result in sodium and/or potassium or magnesium retention (see WARNINGS). Avoid Multiple Electrolytes Injection, Type 1, USP in patients with severe renal impairment or conditions that may cause sodium and/or potassium retention or magnesium retention, fluid overload, or edema. If use cannot be avoided, monitor patients with severe renal impairment for development of these adverse reactions.

Drug Interactions

Other Products that Affect Fluid and/or Electrolyte Balance

Administration of Multiple Electrolytes Injection, Type 1, USP to patients treated concomitantly with drugs associated with sodium and fluid retention, may increase the risk of hypernatremia and volume overload. Avoid use of Multiple Electrolytes Injection, Type 1, USP in patients receiving such products, such as corticosteroids or corticotropin. If use cannot be avoided, monitor serum electrolytes, fluid balance and acid-base balance.

Other Drugs that Increase the Risk of Hyponatremia

Administration of Multiple Electrolytes Injection, Type 1, USP in patients treated concomitantly with medications associated with hyponatremia may increase the risk of developing hyponatremia.

Avoid use of Multiple Electrolytes Injection, Type 1, USP in patients receiving products, such as diuretics, and certain antiepileptic and psychotropic medications. Drugs that increase the vasopressin effect reduce renal electrolyte free water excretion and may also increase the risk of hyponatremia following treatment with intravenous fluids. If use cannot be avoided, monitor serum sodium concentrations.

Lithium

Renal clearance of lithium may be increased during administration of Multiple Electrolytes Injection, Type 1, USP. Monitor serum lithium concentrations during concomitant use.

Other Products that Increase the Risk of Hyperkalemia

Because of its potassium content, avoid use of Multiple Electrolytes Injection, Type 1, USP in patients receiving products that can cause hyperkalemia or increase the risk of hyperkalemia, such as potassium sparing diuretics, ACE inhibitors, angiotensin II receptor antagonists, or the immunosuppressants tacrolimus and cyclosporine. If use cannot be avoided, monitor serum potassium concentrations.

Drugs with pH Dependent Renal Elimination

Due to its alkalinizing effect (formation of bicarbonate), Multiple Electrolytes Injection, Type 1, USP may interfere with the elimination of drugs with pH dependent renal elimination. Renal clearance of acidic drugs may be increased. Renal clearance of alkaline drugs may be decreased.

Drug/Laboratory Test Interactions

There have been reports of positive test results using the Bio-Rad Laboratories Platelia Aspergillus EIA test in patients receiving gluconate containing Multiple Electrolytes Injection, Type 1, USP solutions. These patients were subsequently found to be free of Aspergillus infection. Therefore, positive test results for this test in patients receiving gluconate containing Multiple Electrolytes Injection, Type 1, USP solutions should be interpreted cautiously and confirmed by other diagnostic methods.

Carcinogenesis, Mutagenesis, Impairment of Fertility

Studies with Multiple Electrolytes Injection, Type 1, USP have not been performed to evaluate carcinogenic potential, mutagenic potential, or effects on fertility.

Pregnancy

Teratogenic Effects

Animal reproduction studies have not been conducted with Multiple Electrolytes Injection, Type 1, USP. It is also not known whether Multiple Electrolytes Injection, Type 1, USP can cause fetal harm when administered to a pregnant woman or can affect reproduction capacity. Multiple Electrolytes Injection, Type 1, USP should be given to a pregnant woman only if clearly needed.

Nursing Mothers

It is not known whether this drug is excreted in human milk. Because many drugs are excreted in human milk, caution should be exercised when Multiple Electrolytes Injection, Type 1, USP is administered to a nursing mother.

Pediatric Use

The use of Multiple Electrolytes Injection, Type 1, USP in pediatric patients is based on clinical practice.

Geriatric Use

Geriatric patients are at increased risk of developing electrolyte imbalances. Multiple Electrolytes Injection, Type 1, USP is known to be substantially excreted by the kidney, and the risk of toxic reactions to this drug may be greater in patients with impaired renal function. Therefore, dose selection for an elderly patient should be cautious, usually starting at the low end of the dosing range, reflecting the greater frequency of decreased hepatic, renal, or cardiac function, and of concomitant disease or other drug therapy. Consider monitoring renal function in elderly patients.

ADVERSE REACTIONS

Post-Marketing Adverse Reactions

The following adverse reactions associated with the use of Multiple Electrolytes Injection, Type 1, USP were identified in clinical trials or postmarketing reports. Because postmarketing reactions were reported voluntarily from a population of uncertain size, it is not always possible to estimate their frequency, reliably, or to establish a causal relationship to drug exposure.

Hypersensitivity and Infusion Reactions: tachycardia, chest pain, chest discomfort, dyspnea, flushing, hyperemia, asthenia, pyrexia, hypotension, wheezing, urticaria, cold sweat, chills.

General Disorders and Administration Site Conditions: infusion site pain, burning sensation.

Metabolism and nutrition disorders: hyperkalemia, hyponatremia.

Nervous System Disorders: hyponatremic encephalopathy.

To report SUSPECTED ADVERSE REACTIONS, contact Fresenius Kabi USA, LLC at 1-800-551-7176 or FDA at 1-800-FDA-1088 or www.fda.gov/medwatch.

OVERDOSAGE

Excessive administration of Multiple Electrolytes Injection, Type 1, USP, pH 7.4 can cause:

- fluid overload with a risk of edema (peripheral and/or pulmonary), particularly when renal sodium excretion is impaired.
- hypernatremia and hyperkalemia, especially in patients with severe renal impairment.
- hypermagnesemia. See WARNINGS and ADVERSE REACTIONS
- metabolic alkalosis with or without hypokalemia and decreased ionized serum calcium and magnesium concentrations.

When assessing an overdose, any additives in the solution must also be considered. The effects of an overdose may require immediate medical attention and treatment.

Interventions include discontinuation of Multiple Electrolytes Injection, Type 1, USP, pH 7.4, dose reduction, and other measures as indicated for the specific clinical constellation (e.g., monitoring of fluid balance, electrolyte concentrations and acid base balance).

DOSAGE AND ADMINISTRATION

Important Administration Instructions

- Multiple Electrolytes Injection, Type 1, USP, pH 7.4 is intended for intravenous administration using sterile equipment.
- Do not connect flexible plastic containers in series in order to avoid air embolism due to possible residual air contained in the primary container.
- Set the vent to the closed position on a vented intravenous administration set to prevent air embolism.
- Use a dedicated line without any connections to avoid air embolism.
- Do not pressurize intravenous solutions contained in flexible plastic containers to increase flow rates in order to avoid air embolism due to incomplete evacuation of residual air in the container.
- Prior to infusion, visually inspect the solution for particulate matter and discoloration. The solution should be clear and there should be no precipitates. Do not administer unless solution is clear, and container is undamaged.
- Multiple Electrolytes Injection, Type 1, USP, pH 7.4 is compatible with blood or blood components. It may be administered prior to or following the infusion of blood through the same administration set (i.e., as a priming solution), added to or infused concurrently with blood components, or used as a diluent in the transfusion of packed erythrocytes. Multiple Electrolytes Injection, Type 1, USP, pH 7.4 and 0.9% Sodium Chloride Injection, USP are equally compatible with blood or blood components.

Dosing Information

The choice of product, dosage, volume, rate, and duration of administration is dependent upon the age, weight and clinical condition of the patient and concomitant therapy, and administration should be determined by a physician experienced in intravenous fluid therapy.

Introduction of Additives

Additives may be incompatible.

Evaluate all additions to the plastic container for compatibility and stability of the resulting preparation. Consult with a pharmacist, if available. If, in the informed judgment of the physician, it is deemed advisable to introduce additives, use aseptic technique. Mix thoroughly when additives have been introduced. After addition, if there is a discoloration and/or the appearance of precipitates, insoluble complexes or crystals, do not use. Do not store solutions containing additives. Discard any unused portion.

HOW SUPPLIED

Multiple Electrolytes Injection, Type 1, USP, pH 7.4 in freeflex® plastic containers is available as shown below:

Product Code | Unit of Use | Unit of Sale
389150 | NDC 65219-389-00 One 500 mL freeflex® Bag | NDC 65219-389-05 Package of 20 freeflex® Bags
389100 | NDC 65219-389-02 One 1000 mL freeflex® Bag | NDC 65219-389-10 Package of 10 freeflex® Bags

Exposure of pharmaceutical products to heat should be minimized. Avoid excessive heat. Store at 20° to 25°C (68° to 77°F). [See USP Controlled Room Temperature.]. Brief exposure up to 40°C does not adversely affect the product.

The container closure is not made with natural rubber latex. Non-PVC, Non-DEHP, Sterile.

INSTRUCTIONS FOR USE

For Information on Risk of Air Embolism – see DOSAGE AND ADMINISTRATION.

Check solution container composition, lot number, and expiry date.

Parenteral drug products should be inspected visually for particulate matter and discoloration prior to administration, whenever solution and container permit.

Do not use solution containers in series connections.

Do not remove solution container from its overwrap until immediately before use.

The intact port caps provide visual tamper evidence. Do not use if a port cap is prematurely removed. Maintain strict aseptic technique during handling.

TO OPEN

1. Always inspect the solution container before and after removal from the overwrap.
2. Place the solution container on a clean, flat surface. Using the pre-cut corner tabs, peel open the overwrap and remove the solution container from the overwrap.
3. Check the solution container for leaks by squeezing firmly. If leaks are found, discard as sterility may be impaired.
4. Do not use if the solution is cloudy or a precipitate is present.

TO PREPARE FOR ADMINISTRATION

1. Immediately before inserting the infusion set, break off BLUE Infusion Port Cap with the arrow pointing away from the solution container.
2. Use a non-vented infusion set or close the air-inlet on a vented set.
3. Close the roller clamp of the infusion set.
4. Hold the base of BLUE Infusion Port, twist and push the spike until the spike is fully inserted. Refer to complete directions accompanying set.
5. The BLUE infusion port contains a self‐sealing septum that helps prevent leakage after removing the spike. The infusion port is not intended to be spiked more than once.
6. Suspend solution container from hanger hole.

If supplemental medication is desired, follow directions below.

TO ADD MEDICATION BEFORE SOLUTION ADMINISTRATION

1. Identify WHITE Injection Port with arrow pointing toward solution container.
2. Immediately before injecting additives, break off WHITE Injection Port Cap with the arrow pointing toward solution container.
3. Hold base of WHITE Injection Port.
4. Insert needle (18 to 23 gauge) through the center of WHITE Injection Port's septum and inject additives.
5. Mix solution container contents thoroughly. For high density medication such as potassium chloride, squeeze ports while ports are upright and mix thoroughly.

TO ADD MEDICATION DURING SOLUTION ADMINISTRATION

1. Close the clamp on the set.
2. Identify WHITE Injection Port with arrow pointing toward solution container.
3. Immediately before injecting additives, break off WHITE Injection Port cap with the arrow pointing toward solution container.
4. Hold base of WHITE Injection Port.
5. Insert needle (18 to 23 gauge) through the center of WHITE Injection Port's septum and inject additives.
6. Remove container from IV pole and/or turn to an upright position.
7. Evacuate both ports by squeezing them while container is in the upright position.
8. Mix solution container contents thoroughly.
9. Return container to in use position and continue administration.

For Single Use Only. Discard unused portion.

Manufactured for:

Lake Zurich, IL 60047

Made in Germany

451767

www.fresenius-kabi.com/us

Issued: September 2022

PACKAGE LABEL - PRINCIPAL DISPLAY – Multiple Electrolytes Injection, Type 1, USP pH 7.4 500 mL Bag Label

500 mL

NDC 65219-389-00
Multiple Electrolytes Injection, Type 1, USP pH 7.4

Rx only

Each 100 mL contains: 526 mg Sodium Chloride, USP; 502 mg Sodium Gluconate, USP; 368 mg Sodium Acetate Trihydrate, USP; 37 mg Potassium Chloride, USP; 30 mg Magnesium Chloride, USP

pH adjusted with Sodium Hydroxide.

Electrolytes per 1,000 mL: Sodium 140 mEq; Potassium 5 mEq;

Magnesium 3 mEq; Chloride 98 mEq; Acetate 27 mEq; Gluconate

23 mEq

294 mOsmol/Liter (Calc.) pH 7.4 (6.5 to 8.0)

PACKAGE LABEL – PRINCIPAL DISPLAY – Multiple Electrolytes Injection, Type 1, USP pH 7.4 500 mL Shipper Label

NDC 65219-389-05 389150

Multiple Electrolytes Injection, Type 1, USP pH 7.4

500 mL x 20

STORE AT: 20° to 25°C (68° to 77°F) [see USP Controlled Room Temperature] until ready to use. Avoid excessive heat.

PACKAGE LABEL - PRINCIPAL DISPLAY – Multiple Electrolytes Injection, Type 1, USP pH 7.4 1000 mL Bag Label

1000 mL

NDC 65219-389-02
Multiple Electrolytes Injection, Type 1, USP pH 7.4

Rx only

Each 100 mL contains: 526 mg Sodium Chloride, USP; 502 mg Sodium Gluconate, USP; 368 mg Sodium Acetate Trihydrate, USP; 37 mg Potassium Chloride, USP; 30 mg Magnesium Chloride, USP

pH adjusted with Sodium Hydroxide.

Electrolytes per 1,000 mL: Sodium 140 mEq; Potassium 5 mEq; Magnesium 3 mEq; Chloride 98 mEq; Acetate 27 mEq; Gluconate 23 mEq

294 mOsmol/Liter (Calc.) pH 7.4 (6.5 to 8.0)

PACKAGE LABEL – PRINCIPAL DISPLAY – Multiple Electrolytes Injection, Type 1, USP pH 7.4 1000 mL Shipper Label

NDC 65219-389-10 389100

Multiple Electrolytes Injection, Type 1, USP pH 7.4

1000 mL x 10

STORE AT: 20° to 25°C (68° to 77°F) [see USP Controlled Room Temperature] until ready to use. Avoid excessive heat.